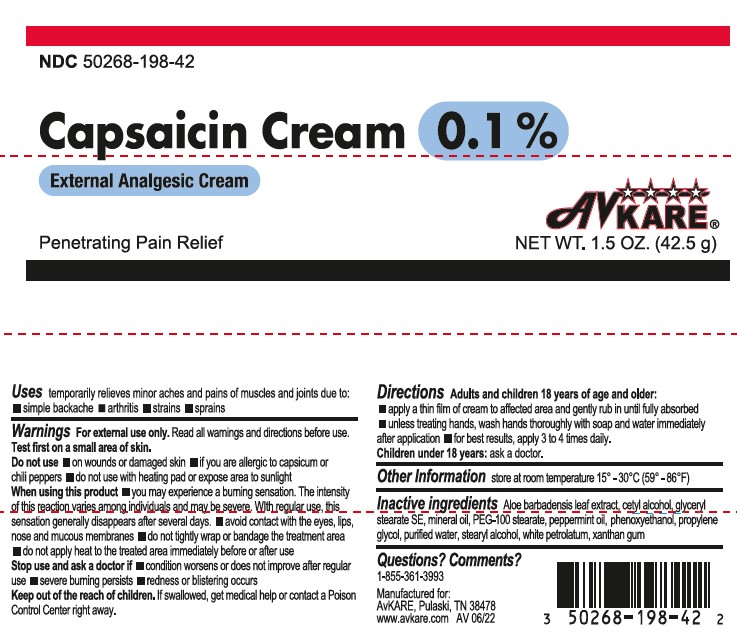 DRUG LABEL: Capsaicin
NDC: 50268-198 | Form: CREAM
Manufacturer: AvPAK
Category: otc | Type: HUMAN OTC DRUG LABEL
Date: 20260108

ACTIVE INGREDIENTS: CAPSAICIN 0.1 g/100 g
INACTIVE INGREDIENTS: CETYL ALCOHOL; ALOE VERA LEAF; XANTHAN GUM; MINERAL OIL; STEARYL ALCOHOL; WATER; PETROLATUM; GLYCERYL STEARATE SE; PROPYLENE GLYCOL; PEPPERMINT OIL; GLYCERYL STEARATE/PEG-100 STEARATE; PHENOXYETHANOL

Capsaicin Cream 0.1%

Active Ingredient

Capsaicin 0.1%

Purpose

Topical Analgesic

Warnings

For external use only: Read all warnings and directions before use. Test first on small area of skin.

Do not use:

- on wounds or damaged skin
- if you are allergic to capsicum or chili peppers
- do not use with heating pad or expose area to sunlight

When using this product:

- you may experience a burning sensation. The intensity of this reaction varies among individuals and may be severe. With regular use, this sensation generally disappears after several days.
- avoid contact with the eyes, lips, nose and mucous membranes
- do not tightly wrap or bandage the treatment area
- do not apply heat to the treated area immediately before or after use

Stop Use and Ask Doctor

Stope Use and Ask Doctor if:

- Condition worsens or does not improve after regular use
- severe burning persists
- redness or blistering occurs

Keep out of the reach of children. If swallowed, get medical help or contact a Poison Control Center right away.

Uses

Temporarily relieves minor aches and pains of muscles and joints due to:

- simple backache
- arthritis
- strains
- sprains

Directions

Adults and Children 18 years of age and older:

- apply a thin film of cream to affected area and gently rub in until fully absorbed
- unless treating hands, wash hands thoroughly with soap and water immediately after application
- for best results, apply 3 to 4 times daily

Children under 18 years:

Ask a doctor

Inactive Ingredients

Aloe barbadensis leaf extract, cetyl alcohol, glyceryl stearate SE, mineral oil, PEG-100 stearate, peppermint oil, phenoxyethanol, propylene glycol, purified water, stearyl alcohol, white petrolatum, xanthan gum

Questions

Questions? Comments?

1-855-361-3993

Manufactured for:

AvKARE, Pulaski, TN 38478

www.avkare.com

AV 06/22

Other Information

Store at room temperature 15°-30°F (59°-86°F)